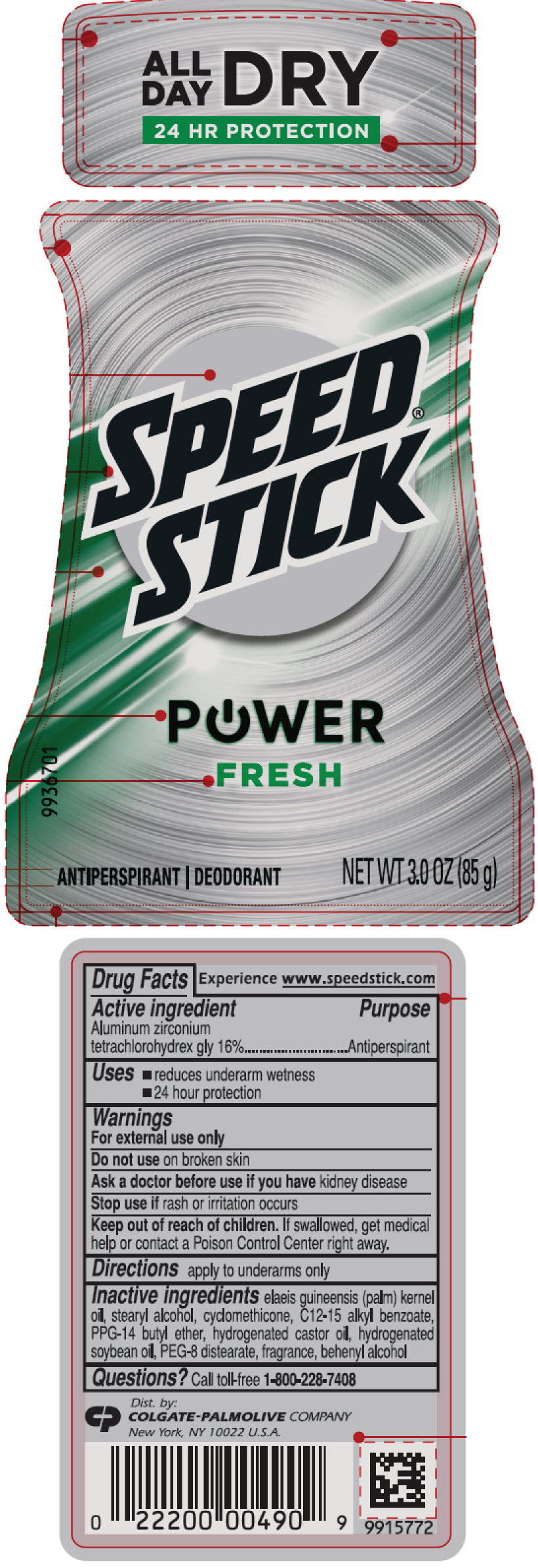 DRUG LABEL: Speed Stick
NDC: 35000-871 | Form: STICK
Manufacturer: Colgate-Palmolive Company
Category: otc | Type: HUMAN OTC DRUG LABEL
Date: 20241029

ACTIVE INGREDIENTS: ALUMINUM ZIRCONIUM TETRACHLOROHYDREX GLY 160 mg/1 g
INACTIVE INGREDIENTS: PALM KERNEL OIL; STEARYL ALCOHOL; CYCLOMETHICONE; ALKYL (C12-15) BENZOATE; PPG-14 BUTYL ETHER; HYDROGENATED CASTOR OIL; HYDROGENATED SOYBEAN OIL; PEG-8 DISTEARATE; DOCOSANOL

Speed
stick®
POWER™
FRESH

Drug Facts

Active ingredient

Aluminum zirconium tetrachlorohydrex gly 16%

Purpose

Antiperspirant

Use

- reduces underarm wetness

Warnings

For external use only

Do not use on broken skin

Ask a doctor before use if you have kidney disease

Stop use if rash or irritation occurs

Keep out of reach of children. If swallowed, get medical help or contact a Poison Control Center right away.

Directions

apply to underarms only

Inactive ingredients

elaeis guineensis (palm) kernel oil, stearyl alcohol, cyclomethicone, C12-15 alkyl benzoate, PPG-14 butyl ether, hydrogenated castor oil, hydrogenated soybean oil, PEG-8 distearate, fragrance, behenyl alcohol

Questions?

Call toll-free 1-800-228-7408

Dist. by:
COLGATE-PALMOLIVE COMPANY
New York, NY 10022

PRINCIPAL DISPLAY PANEL - 85 g Container Label

SPEED®
STICK

POWER
FRESH
9936701

ANTIPERSPIRANT | DEODORANT
NET WT 3.0 OZ (85 g)